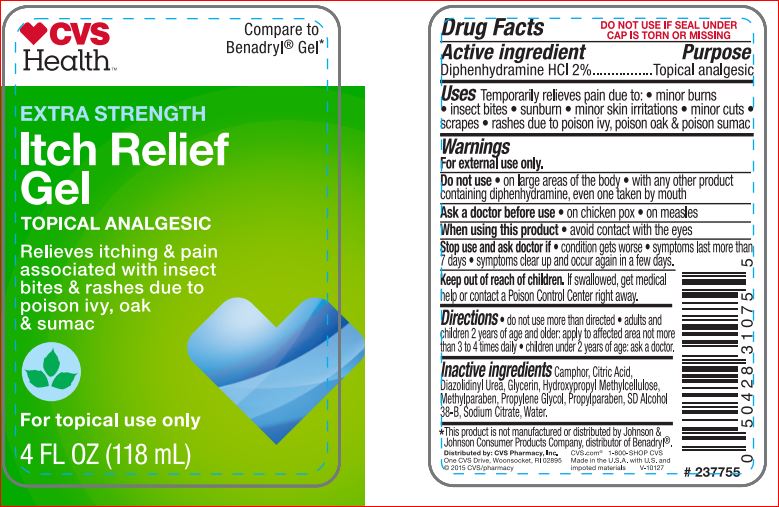 DRUG LABEL: ITCH RELIF
NDC: 69842-038 | Form: GEL
Manufacturer: CVS
Category: otc | Type: HUMAN OTC DRUG LABEL
Date: 20171204

ACTIVE INGREDIENTS: DIPHENHYDRAMINE HYDROCHLORIDE 2 g/100 mL
INACTIVE INGREDIENTS: ALCOHOL; CAMPHOR (SYNTHETIC); CITRIC ACID MONOHYDRATE; Diazolidinyl Urea; Glycerin; HYPROMELLOSES; Methylparaben; Propylene Glycol; Propylparaben; Water; Sodium Citrate

Drug Facts

Active ingredient Purpose
Diphenhydramine HCI 2%................Topical analgesic

Uses

Temporarily relieves pain due to: • minor burns • insect bites • sunburn • minor skin irritations • minor cuts • scrapes • rashes due to poison ivy, poison oak & poison sumac

Directions

• do not use more than directed • adults and children 2 years of age and older: apply to affected area not more than 3 to 4 times daily • children under 2 years of age: ask a doctor.

Warnings
For external use only.
Do not use • on large areas of the body • with any other product containing diphenhydramine, even one taken by mouth

Ask a doctor before use • on chicken pox • on measles

When using this product • avoid contact with the eyes
Stop use and ask doctor if • condition gets worse • symptoms last more than 7 days • symptoms clear up and occur again in a few days.
Keep out of reach of children. If swallowed, get medical help or contact a Poison Control Center right away.

Inactive ingredients:

Camphor
Citric Acid
Diazolidinyl Urea
Glycerin
Hydroxypropyl Methylcellulose
Methylparaben
Propylene Glycol
Propylparaben
SD Alcohol 38-B
Sodium Citrate
Water